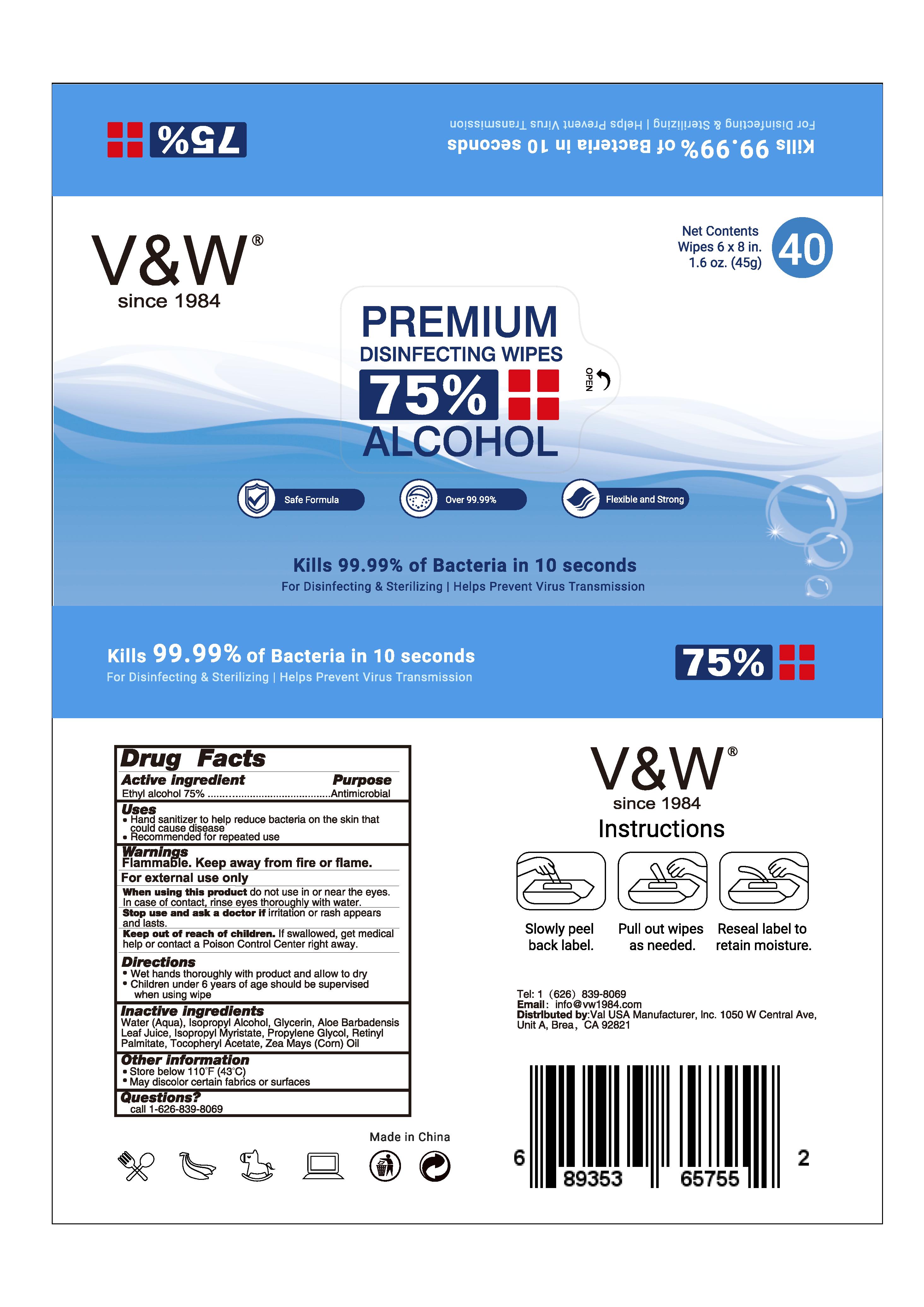 DRUG LABEL: V W
NDC: 75239-007 | Form: CLOTH
Manufacturer: Guangzhou Youxing Cosmetics CO.,LTD
Category: otc | Type: HUMAN OTC DRUG LABEL
Date: 20200711

ACTIVE INGREDIENTS: ALCOHOL 75 mL/100 mL
INACTIVE INGREDIENTS: WATER; ISOPROPYL ALCOHOL; .ALPHA.-TOCOPHEROL ACETATE; GLYCERIN; ALOE VERA LEAF; ISOPROPYL MYRISTATE; PROPYLENE GLYCOL; VITAMIN A PALMITATE; CORN OIL

Youxing-wipe

Active Ingredient(s)

Isopropyl alcohol 75% v/v

Purpose

Antimicrobial

Use

Hand sanitizer to help reduce bacteria on the skin

Warnings

Flammable. Keep away from fire or flame. For external use only

When using this product do not use in or near the eyes. In case of contact, rinse eyes thoroughly with water.

Stop use and ask a doctor if irritation or rash appears and lasts

Keep out of reach of children. If swallowed, get medical help or contact a Poison Control Center right away.

Directions

• Wet hands thoroughly with product and allow to dry

• Children under 6 years of age should be supervised when using wipe

Other information

• Wet hands thoroughly with product and allow to dry

• Children under 6 years of age should be supervised when using PURELL® products

Inactive ingredients

Water (Aqua), Isopropyl Alcohol, Glycerin, Aloe Barbadensis Leaf Juice, Isopropyl Myristate, Propylene Glycol, Retinyl Palmitate, Tocopheryl Acetate, Zea Mays (Corn) Oil

Package Label - Principal Display Panel

40 Cloth in one bag (75239-007-01)